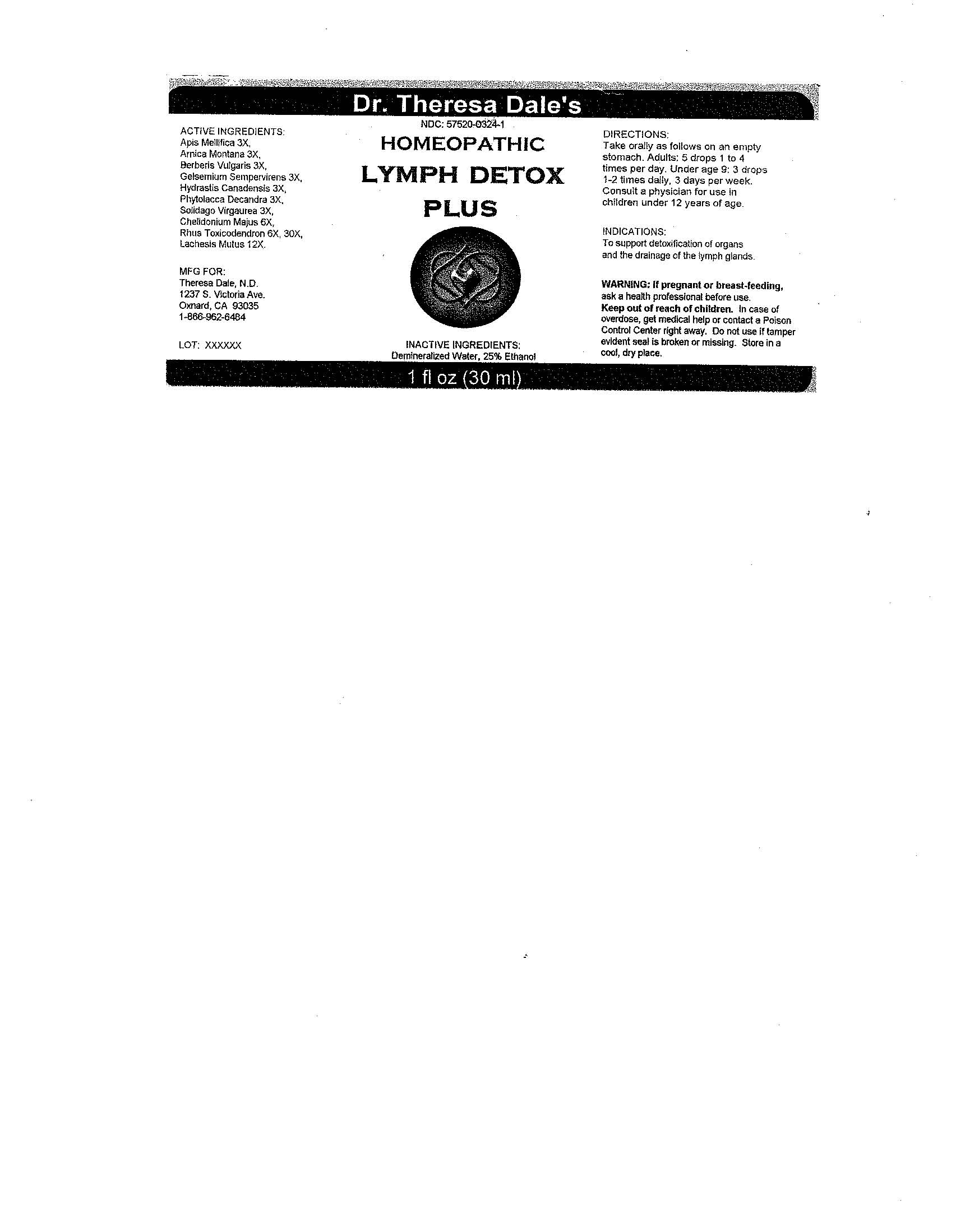 DRUG LABEL: Lymph Detox Plus
NDC: 57520-0324 | Form: LIQUID
Manufacturer: Apotheca Company
Category: homeopathic | Type: HUMAN OTC DRUG LABEL
Date: 20100723

ACTIVE INGREDIENTS: APIS MELLIFERA 3 [hp_X]/1 mL; ARNICA MONTANA 3 [hp_X]/1 mL; BERBERIS VULGARIS ROOT BARK 3 [hp_X]/1 mL; GELSEMIUM SEMPERVIRENS ROOT 3 [hp_X]/1 mL; GOLDENSEAL 3 [hp_X]/1 mL; PHYTOLACCA AMERICANA ROOT 3 [hp_X]/1 mL; SOLIDAGO VIRGAUREA FLOWERING TOP 3 [hp_X]/1 mL; CHELIDONIUM MAJUS 6 [hp_X]/1 mL; TOXICODENDRON PUBESCENS LEAF 30 [hp_X]/1 mL; LACHESIS MUTA VENOM 12 [hp_X]/1 mL
INACTIVE INGREDIENTS: WATER; ALCOHOL

Lymph Detox Plus

ACTIVE INGREDIENT

ACTIVE INGREDIENTS: Apis mellifica 3X, Arnica montana 3X, Berberis vulgaris 3X, Gelsemium sempervirens 3X, Hydrastis canadensis 3X, Phytolacca decandra 3X, Solidago virgaurea 3X, Chelidonium majus 6X, Rhus toxicodendron 6X, 30X, Lachesis mutus 12X.

PURPOSE

INDICATIONS: To support detoxification of organs and the drainage of the lymph glands.

WARNINGS

WARNINGS: If pregnant or breast-feeding, ask a health professional before use.

Keep out of reach of children. In case of overdose, get medical help or contact a Poison Control Center right away.

Do not use if tamper evident seal is broken or missing. Store in a cool, dry place.

DOSAGE AND ADMINISTRATION

DIRECTIONS: Take orally as follows on an empty stomach. Adults: 5 drops 1 to 4 times per day. Under age 9: 3 drops 1-2 times daily, 3 days per week. Consult a physician for use in children under 12 years of age.

INACTIVE INGREDIENTS: Demineralized water, 25% Ethonol

QUESTIONS

MFG. FOR:

Theresa Dale, N.D.

1237 S. Victoria Ave

Oxnard, CA 93035

1-866-962-6484

PACKAGE LABEL

Dr. Theresa Dale's

HOMEOPATHIC

LYMPH DETOX PLUS

1 fl oz (30 ml)